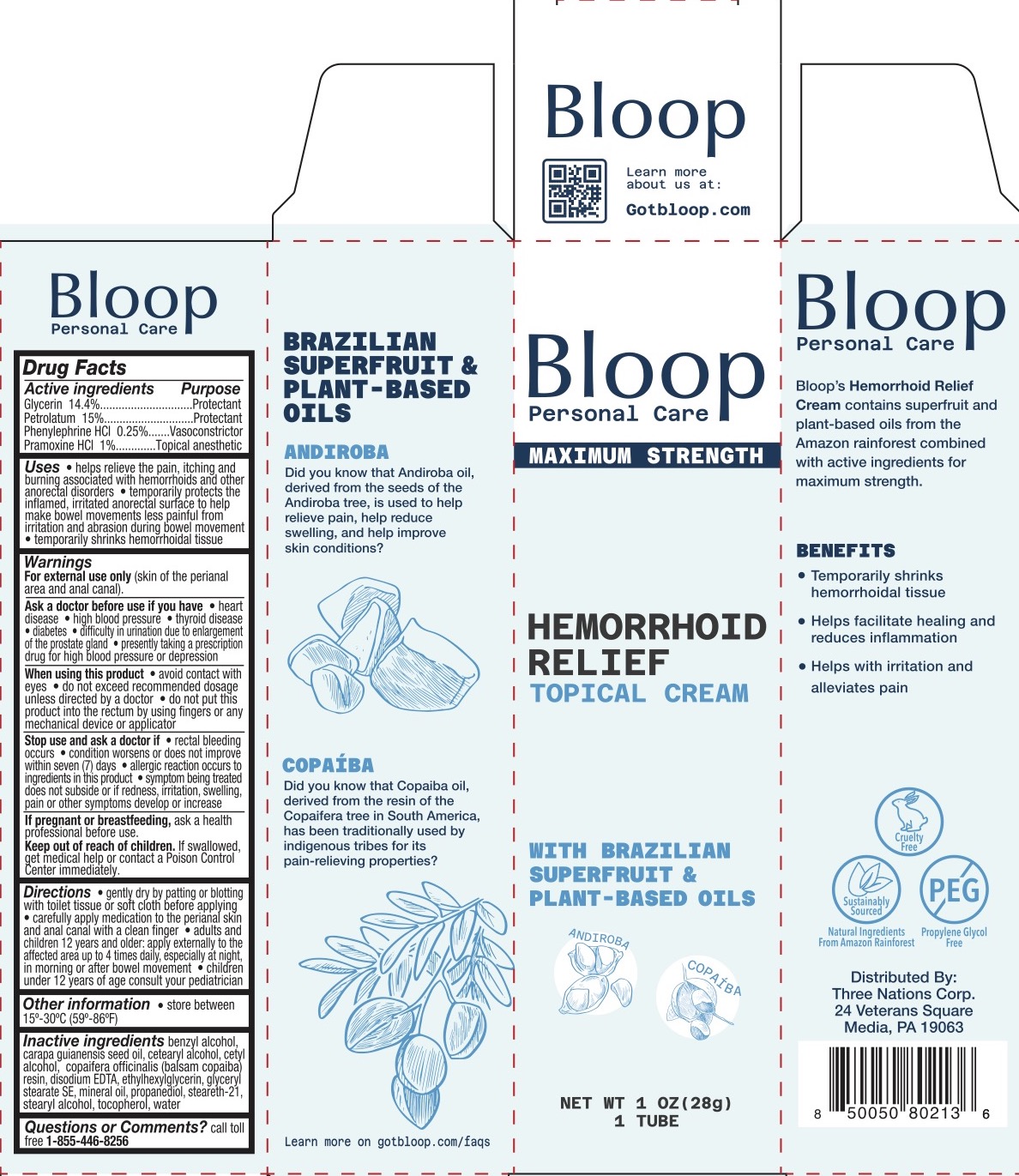 DRUG LABEL: Bloop Hemorrhoid Relief Topical
NDC: 83838-155 | Form: CREAM
Manufacturer: Three Nations Corp
Category: otc | Type: HUMAN OTC DRUG LABEL
Date: 20231130

ACTIVE INGREDIENTS: GLYCERIN 14.4 g/100 g; PRAMOXINE HYDROCHLORIDE 1 g/100 g; PETROLATUM 15 g/100 g; PHENYLEPHRINE HYDROCHLORIDE, (+/-)- 0.25 g/100 g
INACTIVE INGREDIENTS: CETOSTEARYL ALCOHOL; BENZYL ALCOHOL; COPAIFERA OFFICINALIS RESIN; GLYCERYL STEARATE SE; EDETATE DISODIUM; ETHYLHEXYLGLYCERIN; PROPANEDIOL; CETYL ALCOHOL; STEARETH-21; CARAPA GUIANENSIS SEED OIL; STEARYL ALCOHOL; WATER; MINERAL OIL; TOCOPHEROL

Bloop Hemorrhoid Relief Topical Cream

ACTIVE INGREDIENT

Glycerin 14.4%, Petrolatum 15%, Phenylephrine HCl 0.25%, Pramoxine HCl 1%

PURPOSE

Anorectal (hemorrhoidal)

INDICATIONS AND USAGE

- Helps relieve the pain, itching, and burning associated with hemorrhoids and other anorectal disorders
- Temporarily protects the inflamed, irritated anorectal surface to help make bowel movements less painful from irritation and abrasion during bowel movement.
- Temporarily shrinks hemorrhoidal tissue.

WARNINGS

For external use only (skin of the perianal area and anal canal).

Ask a doctor before use if you have

- heart disease
- high blood pressure
- thyroid disease
- diabetes
- difficulty in urination due to enlargement of the prostate gland
- presently taking a prescription drug for high blood pressure or depression

When using this product

- avoid contact with eyes
- do not exceed recommended dosage unless directed by a doctor
- do not put this product into the rectum by using fingers or any mechanical device or applicator

PREGNANCY OR BREAST FEEDING

Ask a health professional before use.

KEEP OUT OF REACH OF CHILDREN

If swallowed, get medical help or contact a Poison Control Center immediately.

DOSAGE AND ADMINISTRATION

- Gently dry by patting or blotting with toilet tissue or soft cloth before applying
- Carefully apply medication to the perianal skin and anal canal with a clean finger
- Adults and children 12 years and older: apply externally to the affected area up to 4 times daily, especially at night, in morning or after bowel movement
- Children under 12 years of age consult your pediatrician.

INACTIVE INGREDIENT

Benzyl alcohol, carapa guianensis seed oil, cetearyl alcohol, cetyl alcohol, copaifera officinalis (balsam copaiba) resin, disodium EDTA, ethylhexylglycerin, glyceryl stearate SE, mineral oil, propanediol, steareth-21, stearyl alcohol, tocopherol, water